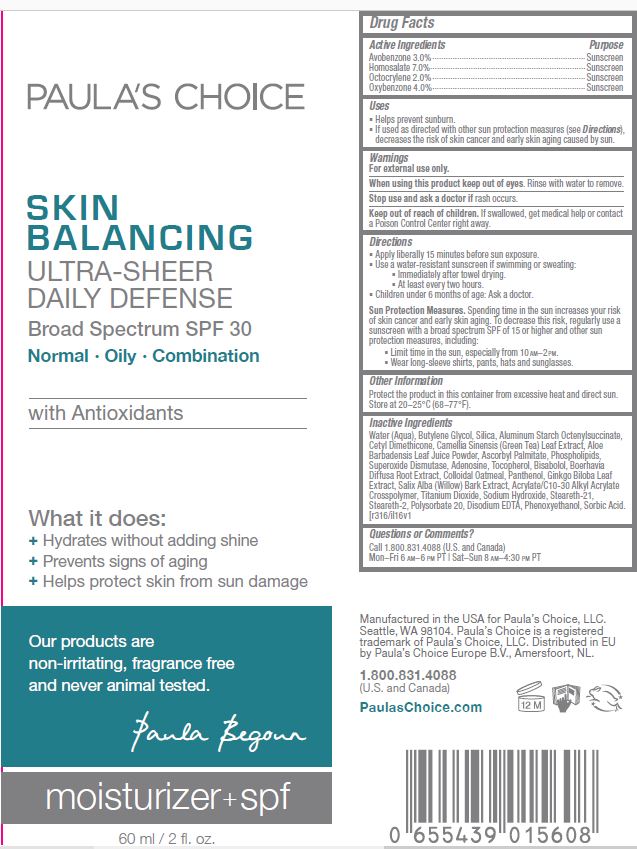 DRUG LABEL: Skin Balancing Ultra Sheer Daily Defence SPF 30
NDC: 56152-5001 | Form: CREAM
Manufacturer: Cosmetic Enterprises Ltd
Category: otc | Type: HUMAN OTC DRUG LABEL
Date: 20251014

ACTIVE INGREDIENTS: AVOBENZONE 3 g/100 mL; HOMOSALATE 7 g/100 mL; OCTOCRYLENE 2 g/100 mL; OXYBENZONE 4 g/100 mL
INACTIVE INGREDIENTS: ALOE VERA LEAF; ASCORBYL PALMITATE; LECITHIN, SOYBEAN; SUPEROXIDE DISMUTASE (SACCHAROMYCES CEREVISIAE); ADENOSINE; TOCOPHEROL; LEVOMENOL; BOERHAVIA DIFFUSA ROOT; OATMEAL; PANTHENOL; GINKGO; SALIX ALBA BARK; CARBOMER INTERPOLYMER TYPE A (ALLYL SUCROSE CROSSLINKED); TITANIUM DIOXIDE; SODIUM HYDROXIDE; STEARETH-21; STEARETH-2; POLYSORBATE 20; EDETATE DISODIUM; PHENOXYETHANOL; SORBIC ACID; WATER; BUTYLENE GLYCOL; SILICON DIOXIDE; ALUMINUM STARCH OCTENYLSUCCINATE; CETYL DIMETHICONE 25; GREEN TEA LEAF

Skin Balancing Broad Spectrum SPF 30

Active Ingredients Purpose

Avobenzone 3.0% ........... Sunscreen
Homosalate 7.0% ............ Sunscreen

Octocrylene 2.0% ............ Sunscreen

Oxybenzone 4.0% ............ Sunscreen

Uses

- Helps prevent sunburn
- If used as directed with other sun protection measures (see Directions), decreases the risk of skin cancer and early skin aging caused by sun.

Keep out of reach of children.If swallowed, get medical help or contact a Poison Control Center right away.

Stop use and ask a doctorif rash occurs

Warnings

For external use only.

When using this product keep out of eyes.Rinse with water to remove.

Directions

- Apply liberally 15 minutes before sun exposure
- Use a water-resistant sunscreen if swimming or sweating:
- Imeediately after towel drying
- At least every two hours
- Children under 6 months of age: Ask a doctor

Sun Protection Measures.Spending time in the sun increases your risk of skin cancer and early skin aging. To decrease this risk, regularly use a sunscreen with a broad spectrum SPF of 15 or higher and other sun protection measures, including:

- Limit time in the sun, especially from 10AM - 2PM
- Wear long-sleeve shirts, pants, hats and sunglasses

INACTIVE INGREDIENT

Water (Aqua), Butylene Glycol, Silica, Aluminum Starch Octenylsuccinate, Cetyl Dimethicone, Camelia Sinensis (Green Tea) Leaf Extract, Aloe Barbadensis Leaf Juice Powder, Ascorbyl Palmitate, Phospholipids, Superoxide Dismutase, Adenosine, Tocopherol, Bisabolol, Boerhavia Diffusa Root Extract, Colloidal Oatmeal, Panthenol, Ginkgo Biloba Leaf Extract, Salix Alba (Willow) Bark Extract, Acrylate/C10-30 Alkyl Acrylate Crosspolymer, Titanium Dioxide, Sodium Hydorxide, Steareth-21, Steareth-2, Polysorbate 20, Disodium EDTA, Phenoxyethanol, Sorbic Acid

PACKAGE LABEL

Paula's Choice

Skin Balancing Ultra-Sheer Daily Defense

Broad Spectrum SPF 30

60ml / 2 fl. oz.